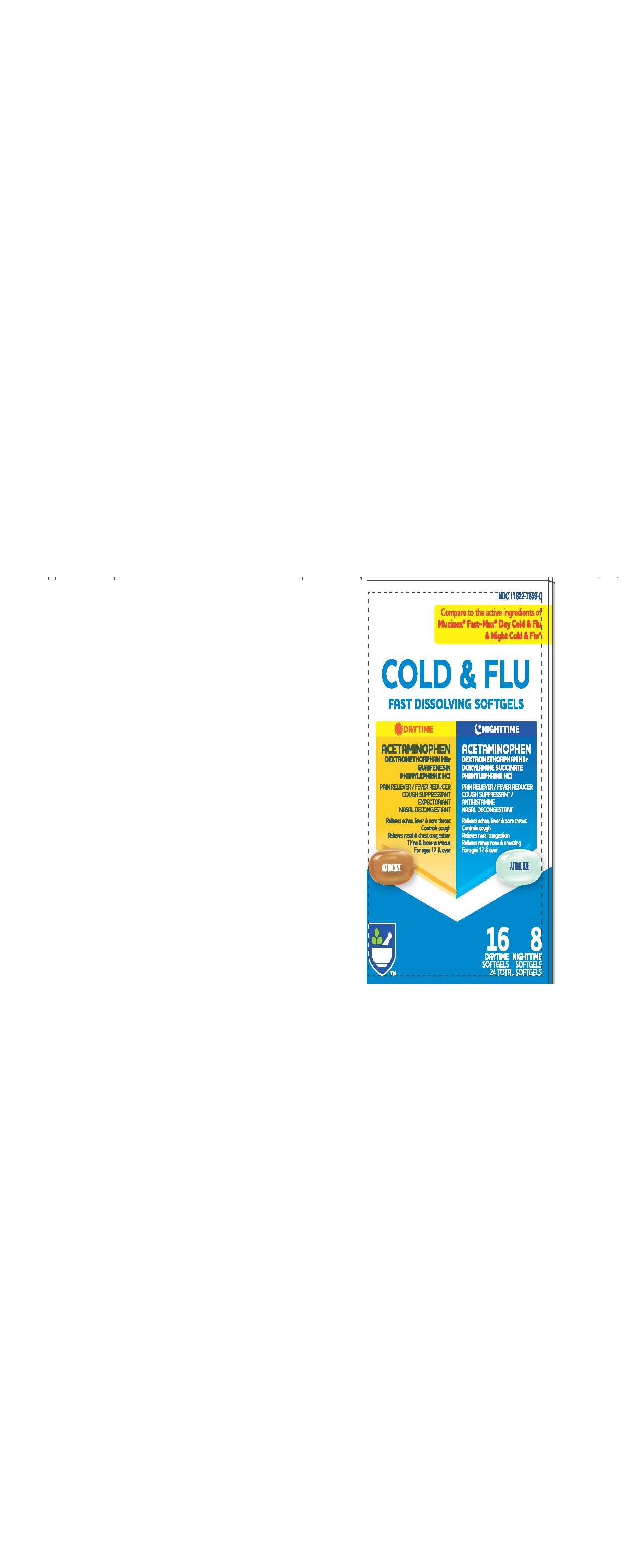 DRUG LABEL: FAST DISSOLVING  DAYTIME - NIGHTTIME COLD AND FLU
NDC: 11822-7859 | Form: KIT | Route: ORAL
Manufacturer: RITE AID
Category: otc | Type: HUMAN OTC DRUG LABEL
Date: 20200818

ACTIVE INGREDIENTS: GUAIFENESIN 200 mg/1 1; ACETAMINOPHEN 325 mg/1 1; PHENYLEPHRINE HYDROCHLORIDE 5 mg/1 1; DEXTROMETHORPHAN HYDROBROMIDE 10 mg/1 1; PHENYLEPHRINE HYDROCHLORIDE 5 mg/1 1; DEXTROMETHORPHAN HYDROBROMIDE 10 mg/1 1; DOXYLAMINE SUCCINATE 6.25 mg/1 1; ACETAMINOPHEN 325 mg/1 1
INACTIVE INGREDIENTS: GELATIN; SHELLAC; POVIDONE; TITANIUM DIOXIDE; FD&C YELLOW NO. 6; PROPYLENE GLYCOL; WATER; POLYETHYLENE GLYCOL, UNSPECIFIED; GLYCERIN; SORBITOL; GLYCERIN; GELATIN; SHELLAC; SORBITOL; POLYETHYLENE GLYCOL, UNSPECIFIED; PROPYLENE GLYCOL; TITANIUM DIOXIDE; FD&C BLUE NO. 1; WATER; POVIDONE

630T RITE AID COLD AND FLU FAST DISSOLVING

Active ingredients (in each softgel)

ACETAMINOPHEN 325MG

DEXTROMETHORHAN HBR10 MG,

GUAIFENESIN 200 MG

, PHENYLEPHRINE HCL 5 MG

INDICATIONS AND USAGE

- temporarily relieves common cold/flu symptoms: nasal congestion,headache, cough, minor aches and pains, sore throat
- temoporarily reducces fever
- prootes nasal and/or sinus drainage
- helps ollsen phlegm (mucus) and thin bronchial secretions to rid the bronchial passageways of bothersome mucus and make coughs more productive

Warnings
Liver warning - This product contains acetaminophen. Severe liver damage may occur if you take - more than 8sogtgels

This product contains acetaminophen.

Severe liver damage may occur if you take:

- more than 8 Softgels in 24 hrs, which is the maximum daily amount for this product
- with other drugs containing acetaminophen
- 3 or more alcoholic drinks every day while using this product

Allergy Alert:

Acetaminophen may cause severe skin reactions. Symptoms may include:

- Skin reddening
- Blisters
- Rash

If a skin reaction occurs, stop use and seek medical help right away

Sore throat warning:

If sore throat is severe, persists for more than 2 days, is accompanied or followed by fever, headache, rash, nausea, or vomiting, consult a doctor promptly.

INACTIVE INGREDIENT

FD&C Yellow #6, gelatin, glycerin, polyethylene glycol, povidone, propylene glycol, purified water, shellac,sorbitol sorbitan solution, titanium dioxide

DOSAGE AND ADMINISTRATION

Do not take more than directed (See Overdose warning section) - do not exceed 12 Softgels per 24 hr period

- adults & children 12 yrs & over 2 Softgels every 4 hrs
- children 4 to under 12 yrs: Do not use

Keep out of reach of children.

Overdose warning: Taking more than the recommended dose (overdose) may cause liver damage.

In case of overdose, get medical help or contact a Poison Control Center right away. (1800-222-1222) Quick medical attention is critical for adults as well as for children even if you do not notice any signs or symptoms.

PURPOSE

PAIN RELIEVER-FEVER REDUCER

COUGH SUPPRESENT

MINOR ACHES AND PAINS

CHEST CONGESTION

ACTIVE INGREDIENT

(in each softgel)
Acetaminophen 325mg

Dextromethorphan HBR 10 mg

Doxylamine Succinate 6.25 mg

PhenylephrineHCl 5mg

Purpose

- Pain reliever/Fever reducer
- Cough suppressant
- Antihistamine
- Nasal decongestant

PURPOSE

MINOR ACHES AND PAINS, FEVER

NASAL CONGESTION AND SINUS PRESSURE

SNEEZING, RUNNY NOSE

COUGH

PURPOSE

PAIN RELIEVER-FEVER REDUCER

COUGH SUPPRESENT

MINOR ACHES AND PAINS

NASAL DECONGESTION

Warnings
Liver warning - This product contains acetaminophen. Severe liver damage may occur if you take

- more than 8 softgels in 24 hrs, which is the maximum daily amount for this product -
- with other drugs containing acetaminophen
- 3 or more alcoholic drinks every day while using this product

Allergy Alert:

Acetaminophen may cause severe skin reactions. Symptoms may include:

- Skin reddening
- Blisters
- Rash

If a skin reaction occurs, stop use and seek medical help right away

Sore throat warning

If sore throat is severe, persists for more than 2 days, is accompanied or followed by fever, headache, rash, nausea, or vomiting, consult a doctor promptly.

Directions
take only as directed - do not exceed 8 softgels per 24 hours -

adults & children 12 yrs & over 2 softgels with water every 6 hrs -

children 4 to under 12 yrs ask a doctor -

children under 4 yrs do not use

INACTIVE INGREDIENT

FD&C Blue No. 1, gelatin, glycerin, polyethylene glycol, povidone, propylene glycol, purified water, shellac, sorbitol sorbitan solution, titanium dioxide

Keep out of reach of children.

Overdose warning

In case of overdose, get medical help or contact a Poison Control Center right away (1-800-222-1222. Quick medical attention is critical for adults as well as for children even if you do not notice any signs or symptoms